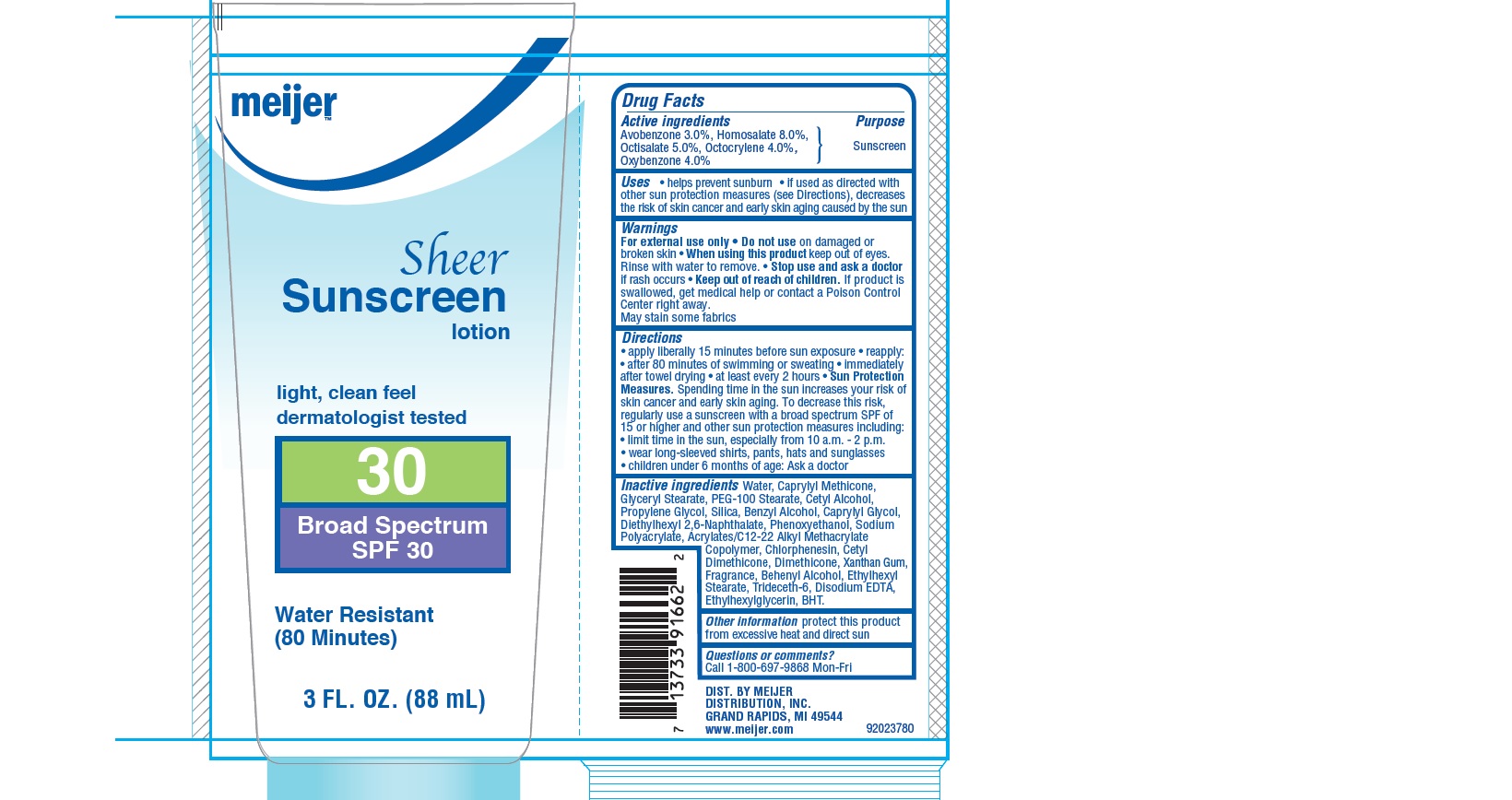 DRUG LABEL: Meijer Sheer SPF 30
NDC: 41250-707 | Form: LOTION
Manufacturer: Meijer Distribution, Inc.
Category: otc | Type: HUMAN OTC DRUG LABEL
Date: 20160531

ACTIVE INGREDIENTS: AVOBENZONE 3 g/100 g; HOMOSALATE  8 g/100 g; OCTISALATE  5 g/100 g; OCTOCRYLENE 4 g/100 g; OXYBENZONE 4 g/100 g
INACTIVE INGREDIENTS: WATER; CAPRYLYL TRISILOXANE; GLYCERYL MONOSTEARATE; PEG-100 STEARATE; CETYL ALCOHOL; PROPYLENE GLYCOL; SILICON DIOXIDE; BENZYL ALCOHOL; CAPRYLYL GLYCOL; DIETHYLHEXYL 2,6-NAPHTHALATE; PHENOXYETHANOL; CHLORPHENESIN; DIMETHICONE; XANTHAN GUM; DOCOSANOL; ETHYLHEXYL STEARATE ; TRIDECETH-6; EDETATE DISODIUM; ETHYLHEXYLGLYCERIN; BUTYLATED HYDROXYTOLUENE

Drug Facts

Active ingredients

Avobenzone 3.0%, Homosalate 8.0%, Octisalate 5.0%, Octocrylene 4.0%, Oxybenzone 4.0%

Purpose

Sunscreen

Uses

• helps prevent sunburn

• if used as directed with other sun protection measures (see Directions), decreases the risk of skin cancer and early skin aging caused by the sun

Warnings

For external use only

Do not use

on damaged or broken skin

When using this product

keep out of eyes. Rinse with water to remove.

Stop use and ask a doctor

if rash occurs

Keep out of reach of children.

If product is swallowed, get medical help or contact a Poison Control Center right away.

- May stain some fabrics

Directions

- apply liberally 15 minutes before sun exposure
- reapply:
- after 80 minutes of swimming or sweating
- immediately after towel drying
- at least every 2 hours
- Sun Protection Measures: Spending time in the sun increases your risk of skin cancer and early skin aging. To decrease this risk, regularly use a sunscreen with a broad spectrum SPF of 15 or higher and other sun protection measures including:
- limit time in the sun, especially from 10 a.m. to 2 p.m.
- wear long-sleeved shirts, pants, hats, and sunglasses
- children under 6 months: Ask a doctor

Inactive Ingredients

Water, Caprylyl Methicone, Glyceryl Stearate, PEG-100 Stearate, Cetyl Alcohol, Propylene Glycol, Silica, Benzyl Alcohol, Caprylyl Glycol, Diethylhexyl 2,6-Naphthalate, Phenoxyethanol, Sodium Polyacrylate, Acrylates/C12-22 Alkyl Methacrylate Copolymer, Chlorphenesin, Cetyl Dimethicone, Dimethicone, Xanthan Gum, Fragrance, Behenyl Alcohol, Ethylhexyl Stearate, Trideceth-6, Disodium EDTA, Ethylhexylglycerin, BHT.

Other information

protect this product from excessive heat and direct sun

Questions or comments?

Call 1-800-697-9868 Mon-Fri

Principle Display Panel

NDC: 41250-707-22

meijer

Sheer

Sunscreen

lotion

light, clean feel

dermatologist tested

30

Broad Spectrum

SPF 30

Water Resistant

(80 minutes)

3 FL. OZ. (88 mL)